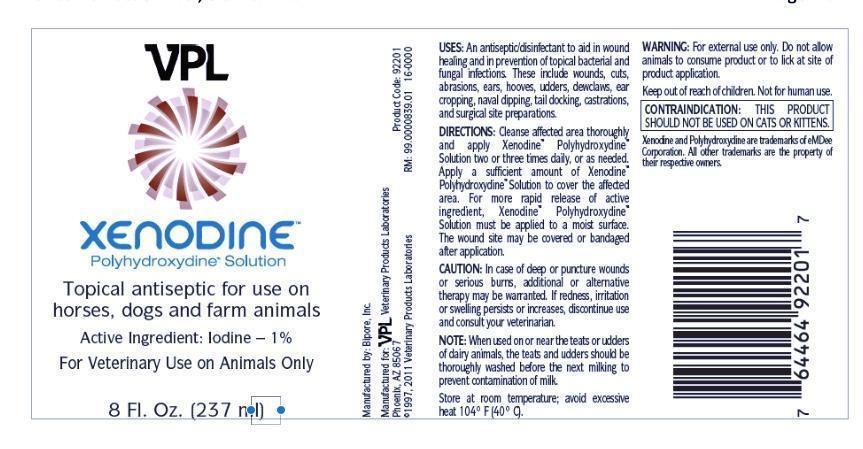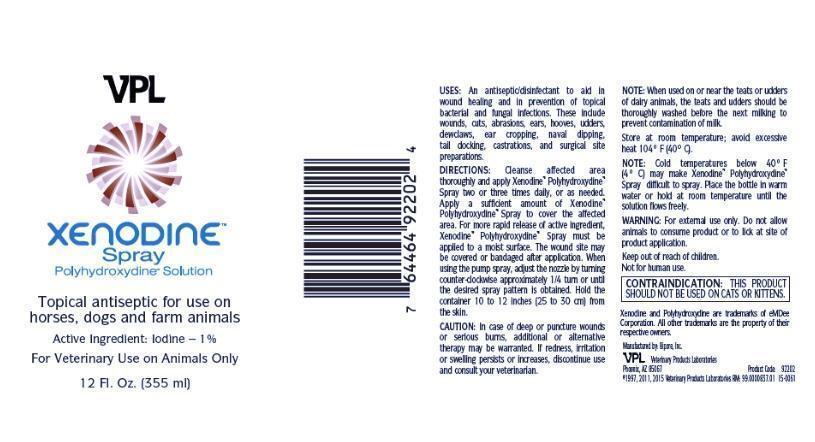 DRUG LABEL: XENODINE
NDC: 86075-001 | Form: SOLUTION
Manufacturer: Bipore Inc
Category: animal | Type: OTC ANIMAL DRUG LABEL
Date: 20161229

ACTIVE INGREDIENTS: IODINE 10 mg/1 mL
INACTIVE INGREDIENTS: PROPYLENE GLYCOL; ETHYLENE GLYCOL

Xenodine

Actives

Iodine 1 %

Inactives

polypropylene glycol and polyethylene glycol